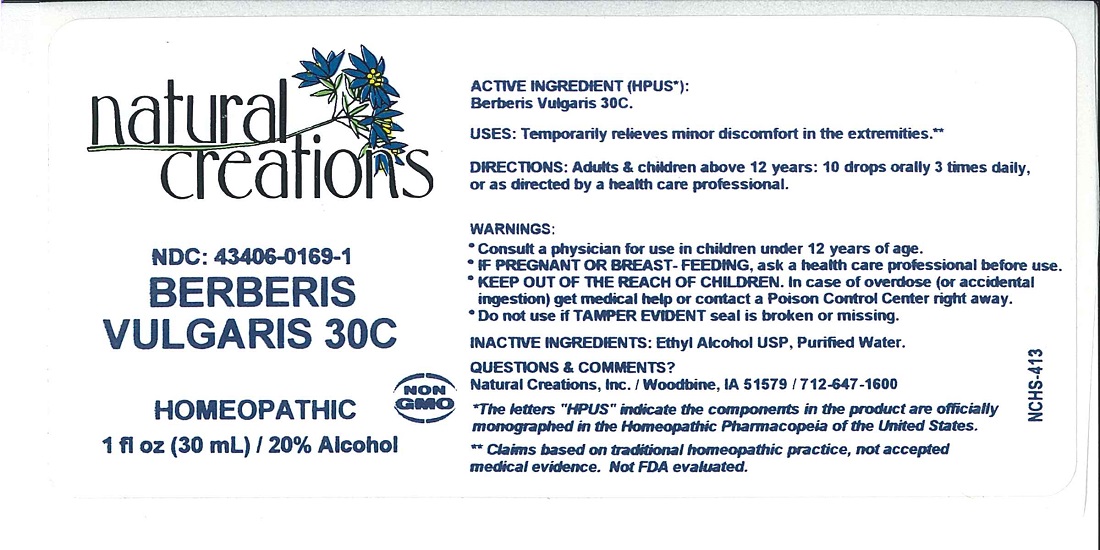 DRUG LABEL: Berberis Vulgaris 30C
NDC: 43406-0169 | Form: LIQUID
Manufacturer: Natural Creations, Inc.
Category: homeopathic | Type: HUMAN OTC DRUG LABEL
Date: 20221219

ACTIVE INGREDIENTS: BERBERIS VULGARIS ROOT BARK 30 [hp_C]/1 mL
INACTIVE INGREDIENTS: ALCOHOL; WATER

BERBERIS VULGARIS 30C

ACTIVE INGREDIENT (HPUS*):

Berberis Vulgaris 30C

PURPOSE

USES: Temporarily relieves minor discomfort in the extremities.**

INDICATIONS AND USAGE

USES: Temporarily relieves minor discomfort in the extremities.**

DOSAGE AND ADMINISTRATION

DIRECTIONS: Adults & children above 12 years: 10 drops orally 3 times daily, or as directed by a health care professional.

KEEP OUT OF REACH OF CHILDREN

KEEP OUT OF THE REACH OF CHILDREN. In case of overdose (or accidental ingestion) get medical help or contact a Poison Control Center right away.

WARNINGS:

- Consult a physician for use in children under 12 years of age.
- IF PREGNANT OR BREAST-FEEDING, ask a health care professional before use.
- KEEP OUT OF THE REACH OF CHILDREN. In case of overdose (or accidental ingestion) get medical help or contact a Poison Control Center right away.
- Do not use if TAMPER EVIDENT seal is broken or missing.

INACTIVE INGREDIENTS: Ethyl Alcohol USP, Purified Water.

QUESTIONS & COMMENTS?

Natural Creations, Inc. / Woodbine, IA 51579 / 712-647-1600

REFERENCES

*The letters "HPUS" indicate the component in the product are officially monographed in the Homeopathic Pharmacopeia of the United States.

**Claims based on traditional homeopathic practice, not accepted medical evidence. Not FDA evaluated.

PACKAGE LABEL

NDC: 43406-0169-1

BERBERIS VULGARIS 30C

HOMEOPATHIC

1 fl oz (30 mL) / 20% Alcohol